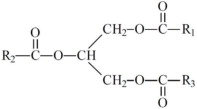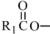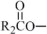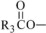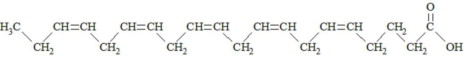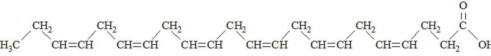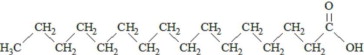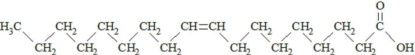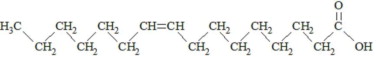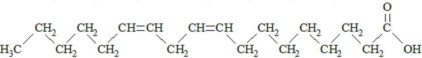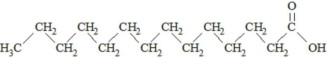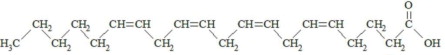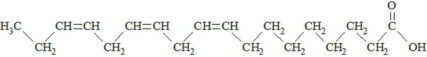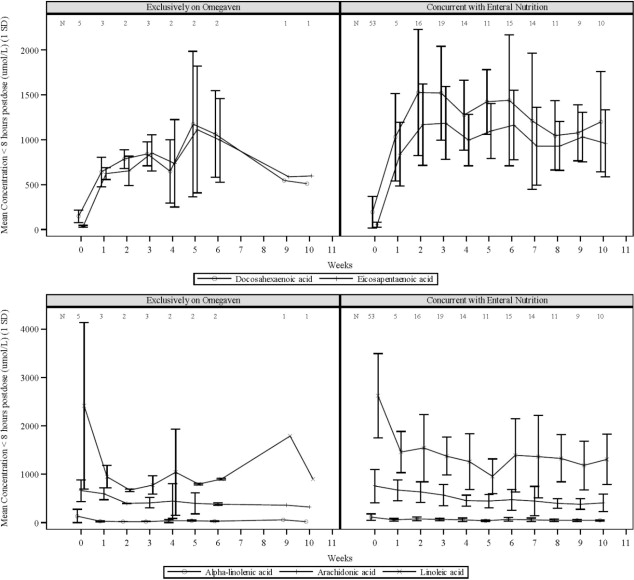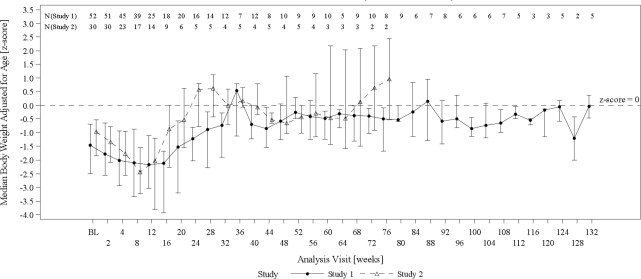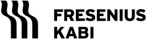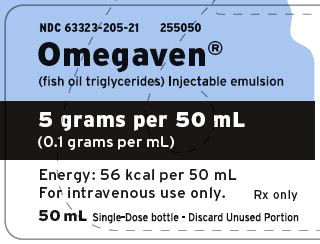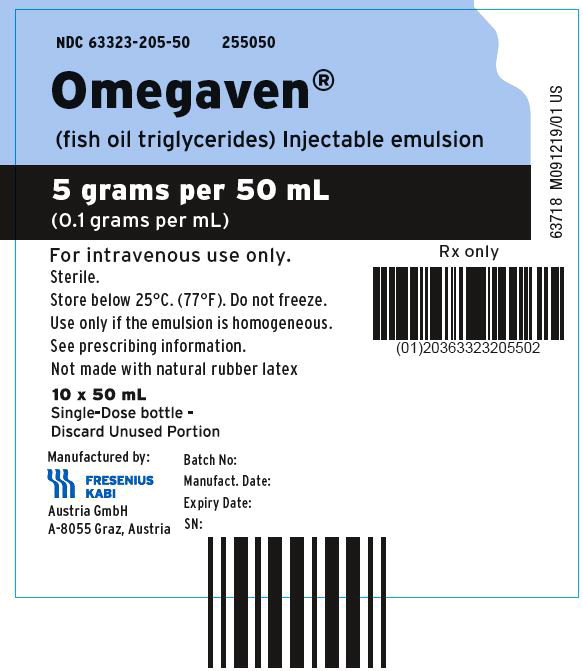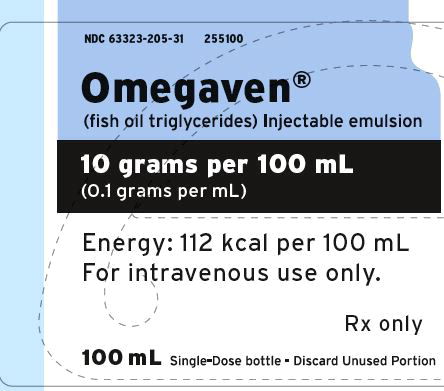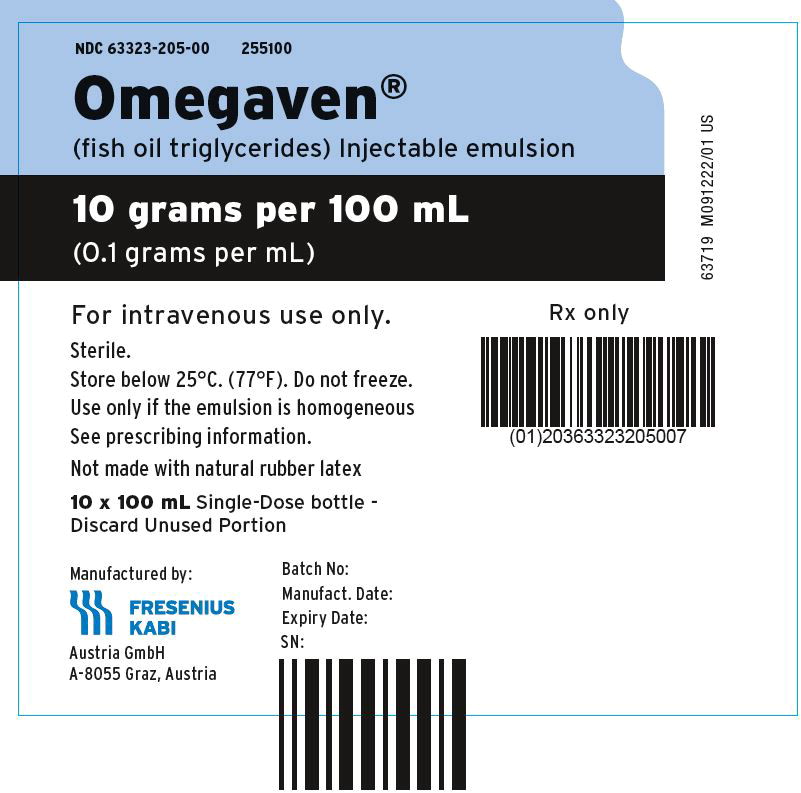 DRUG LABEL: Omegaven
NDC: 63323-205 | Form: INJECTION, EMULSION
Manufacturer: Fresenius Kabi USA, LLC
Category: prescription | Type: HUMAN PRESCRIPTION DRUG LABEL
Date: 20250905

ACTIVE INGREDIENTS: Fish oil 0.1 g/1 mL
INACTIVE INGREDIENTS: .alpha.-tocopherol, dl-; egg phospholipids; sodium oleate; glycerin; sodium hydroxide; water

HIGHLIGHTS OF PRESCRIBING INFORMATION

These highlights do not include all the information needed to use OMEGAVEN safely and effectively. See full prescribing information for OMEGAVEN.
OMEGAVEN (fish oil triglycerides) injectable emulsion, for intravenous use
Initial U.S. Approval: 2018

RECENT MAJOR CHANGES

Warnings and Precautions (5.2) | 7/2025

1 INDICATIONS AND USAGE

Omegaven is indicated as a source of calories and fatty acids in pediatric patients with parenteral nutrition-associated cholestasis (PNAC). (1)

Limitations of Use:

- Omegaven is not indicated for the prevention of PNAC. It has not been demonstrated that Omegaven prevents PNAC in parenteral nutrition (PN)-dependent patients. (1)
- It has not been demonstrated that the clinical outcomes observed in patients treated with Omegaven are a result of the omega-6:omega-3 fatty acid ratio of the product. (1)

2 DOSAGE AND ADMINISTRATION

- For infusion into a central or peripheral vein. (2.1)
- See full prescribing information for administration and admixing instructions. (2.1, 2.2)
- Protect the admixed PN solution from light. (2.2)
- Recommended dosage depends on age, energy expenditure, clinical status, body weight, tolerance, ability to metabolize, and consideration of additional energy sources given to the patient. The recommended daily dose (and the maximum dose) in pediatric patients is 1 g/kg/day. (2.3)
- For information on infusion rate when initiating dosing and in patients with elevated triglyceride levels, see the full prescribing information. (2.3, 5.1, 5.6)
- The recommended duration for infusion is between 8 and 24 hours, depending on the clinical situation. (2.3)

3 DOSAGE FORMS AND STRENGTHS

Injectable Emulsion: 5 g/50 mL and 10 g/100 mL (0.1 g/mL) in a single-dose bottle (3)

4 CONTRAINDICATIONS

- Known hypersensitivity to fish or egg protein or to any of the active ingredients or excipients. (4)
- Severe hemorrhagic disorders. (4)
- Severe disorders of lipid metabolism characterized by hypertriglyceridemia (with serum triglycerides greater than 1,000 mg/dL). (4, 5.6)

5 WARNINGS AND PRECAUTIONS

- Clinical Decompensation with Rapid Infusion of Intravenous Lipid Emulsion in Neonates and Infants: Acute respiratory distress, metabolic acidosis, and death after rapid infusion of intravenous lipid emulsions have been reported. (5.1)
- Hypersensitivity Reactions: Monitor for signs or symptoms. Discontinue infusion if reaction occurs. (5.2)
- Risk of Infections, Fat Overload Syndrome, Refeeding Syndrome, and Hypertriglyceridemia: Monitor for signs and symptoms; monitor laboratory parameters. (5.3, 5.4, 5.5, 5.6)
- Aluminum Toxicity: Increased risk in patients with renal impairment, including preterm infants. (5.7)
- Monitoring and Laboratory Tests: Routine laboratory monitoring is recommended, including monitoring for essential fatty acid deficiency. (5.8)

6 ADVERSE REACTIONS

Most common adverse drug reactions (>15%) are: vomiting, agitation, bradycardia, apnea and viral infection. (6.1)

To report SUSPECTED ADVERSE REACTIONS, contact Fresenius Kabi USA, LLC at 1-800-551-7176 or FDA at 1-800-FDA-1088 or www.fda.gov/medwatch.

7 DRUG INTERACTIONS

Antiplatelet Agents and Anticoagulants: Prolonged bleeding time has been reported in patients taking antiplatelet agents or anticoagulants and oral omega-3 fatty acids. Periodically monitor bleeding time in patients receiving Omegaven and concomitant antiplatelet agents or anticoagulants. (7.1)

FULL PRESCRIBING INFORMATION

1 INDICATIONS AND USAGE

Omegaven is indicated as a source of calories and fatty acids in pediatric patients with parenteral nutrition-associated cholestasis (PNAC).

Limitations of Use:

- Omegaven is not indicated for the prevention of PNAC. It has not been demonstrated that Omegaven prevents PNAC in parenteral nutrition (PN)-dependent patients [see Clinical Studies (14)].
- It has not been demonstrated that the clinical outcomes observed in patients treated with Omegaven are a result of the omega-6: omega-3 fatty acid ratio of the product [see Clinical Studies (14)].

2 DOSAGE AND ADMINISTRATION

2.1 Administration Instructions

- Omegaven can be administered alone or as part of a PN admixture.
- Omegaven is for central or peripheral intravenous infusion. When administered with dextrose and amino acids, the choice of a central or peripheral venous route should depend on the osmolarity of the final infusate. Solutions with osmolarity of 900 mOsm/L or greater must be infused through a central vein.
- Do not exceed the recommended maximum infusion rate in Table 1 [see Dosage and Administration (2.3) and Warnings and Precautions (5.1)].
- Use a 1.2 micron in-line filter during administration.
- Use a dedicated line for PN. Omegaven should be infused concurrently into the same vein as dextrose-amino acid solutions (as part of PN) by a Y-connector located closest to the infusion site; flow rates of each solution should be controlled separately by infusion pumps. Avoid multiple connections; do not connect multiple medications in series. Turn off the pump before the bottle runs dry.
- Use a vented infusion set when Omegaven is infused from the bottle.
- Do not use infusion sets and lines that contain di-2-ethylhexyl phthalate (DEHP). Infusion sets that contain polyvinyl chloride (PVC) components have DEHP as a plasticizer.
- Prior to infusion, visually inspect Omegaven for particulate matter and discoloration. Discard the bottle if any particulates or discoloration are observed.
- Gently invert the bottle before use. Use Omegaven only if the emulsion is homogeneous and the container is undamaged.
- Strict aseptic techniques must be followed.
- Hang the bottle using the attached hanger and start infusion.
- After connecting the infusion set, start infusion of Omegaven immediately. Complete the infusion within 12 hours when using a Y-connector and within 24 hours when used as part of an admixture.
- For single use only. Discard unused portion.

2.2 Admixing Instructions

If Omegaven is administered as part of a PN admixture, follow the instructions below.

- Prepare the admixture in PN containers using strict aseptic techniques to avoid microbial contamination.
- Do not add Omegaven directly to the empty PN container; destabilization of the lipid emulsion may occur.
- When Omegaven is administered with other infusion solutions (e.g., amino acids, dextrose), the compatibility of the solutions used must be ensured. Questions related to compatibility may be directed to Fresenius Kabi USA, LLC, at 1-800-551-7176.
- The following proper mixing sequence must be followed to minimize pH-related problems by ensuring that typically acidic dextrose solutions are not mixed with lipid emulsions alone:
  1. Transfer dextrose solution to the PN container.
  2. Transfer amino acid solution to the PN container.
  3. Transfer Omegaven to the PN container.
Simultaneous transfer of amino acid solution, dextrose solution, and Omegaven using an automated compounding device is also permitted; follow automated compounding device instructions as indicated.
  Use gentle agitation during admixing to minimize localized concentration effects; shake container gently after each addition.
- The prime destabilizers of emulsions are excessive acidity (such as a pH less than 5) and inappropriate electrolyte content. Care should be taken if adding divalent cations (e.g., Ca^++ and Mg^++), which have been shown to cause emulsion instability. Amino acid solutions exert buffering effects that can protect the emulsion from destabilization.
- Inspect the admixture to ensure that precipitates have not formed during preparation of the admixture and the emulsion has not separated. Separation of the emulsion can be visibly identified by a yellowish streaking or the accumulation of yellowish droplets in the admixture. Discard the admixture if any of these are observed.

Stability and Storage

- Protect the admixed PN solution from light.
- Start infusion of admixtures containing Omegaven immediately. If not used immediately, admixtures may be stored for up to 6 hours at room temperature or up to 24 hours under refrigeration. Complete the infusion within 24 hours after removal from storage.
- Any remaining contents of a partly used PN container must be discarded.
- Follow the instructions of each product included in the admixture.

2.3 Dosing Information

Dosing Considerations

- Prior to administration of Omegaven, correct severe fluid and electrolyte disorders and measure serum triglycerides to establish a baseline level.
- Initiate Omegaven dosing as soon as direct or conjugated bilirubin (DBil) levels are 2 mg/dL or greater in pediatric patients who are expected to be PN-dependent for at least 2 weeks.
- The dosing of Omegaven depends on each patient's energy requirements, which may be influenced by age, body weight, tolerance, clinical status, and ability to metabolize and eliminate lipids.
- When determining dose, take into account the energy supplied by dextrose and amino acids from PN, as well as energy from oral or enteral nutrition. Energy provided from lipid-based medications must also be taken into account (e.g., propofol).
- Omegaven contains 0.15 to 0.30 mg/mL of dl-alpha-tocopherol. Take into account the amount of alpha-tocopherol in Omegaven when determining the need for additional supplementation of vitamin E.

Recommended Pediatric Dosing

- The recommended nutritional requirements of fat and recommended dosage of Omegaven to meet those requirements for pediatric patients are provided in Table 1, along with recommendations for the initial and maximum infusion rates.
- If hypertriglyceridemia (triglycerides greater than 250 mg/dL in neonates and infants or greater than 400 mg/dL in older children) develops once Omegaven has been initiated at the recommended dosage, consider stopping the administration of Omegaven for 4 hours and obtain a repeat serum triglyceride level. Resume Omegaven based on new result as indicated.
- In patients with elevated triglyceride levels, consider other reasons for hypertriglyceridemia (e.g., renal disease, other drugs). If triglycerides remain at elevated levels, consider a reduced dose of 0.5 g to 0.75 g/kg/day with an incremental increase to 1 g/kg/day.
- Monitor triglyceride levels during treatment [see Warnings and Precautions (5.6, 5.8)].
- The recommended duration for infusion of Omegaven is between 8 and 24 hours, depending on the clinical situation.
- Administer Omegaven until DBil levels are less than 2 mg/dL or until the patient no longer requires PN.

Table 1: Recommended Pediatric Dosage and Infusion Rate
Nutritional Requirements | Direct Infusion Rate
Recommended Initial Dosage and Maximum Dosage | Initial | Maximum
1 g/kg/day; this is also the maximum daily dose | 0.2 mL/kg/hour for the first 15 to 30 minutes; gradually increase to the required rate after 30 minutes | 1.5 mL/kg/hour

3 DOSAGE FORMS AND STRENGTHS

Injectable Emulsion: 5 g/50 mL and 10 g/100 mL (0.1 g/mL) sterile, white, homogenous emulsion in a 50-mL and 100-mL single-dose bottle.

4 CONTRAINDICATIONS

Use of Omegaven is contraindicated in patients with:

- Known hypersensitivity to fish or egg protein or to any of the active ingredients or excipients [see Warnings and Precautions (5.2)].
- Severe hemorrhagic disorders due to a potential effect on platelet aggregation.
- Severe disorders of lipid metabolism characterized by hypertriglyceridemia (serum triglyceride concentrations greater than 1,000 mg/dL) [see Warnings and Precautions (5.6)].

5 WARNINGS AND PRECAUTIONS

5.1 Clinical Decompensation with Rapid Infusion of Intravenous Lipid Emulsion in Neonates and Infants

In the postmarket setting, serious adverse reactions including acute respiratory distress, metabolic acidosis, and death have been reported in neonates and infants after rapid infusion of intravenous lipid emulsions. Hypertriglyceridemia was commonly reported.

Strictly adhere to the recommended total daily dosage; the hourly infusion rate should not exceed 1.5 mL/kg/hour [see Dosage and Administration (2.3)].

Preterm and small for gestational age infants have poor clearance of intravenous lipid emulsion and increased free fatty acid plasma levels following lipid emulsion infusion.

Carefully monitor the infant's ability to eliminate the infused lipids from the circulation (e.g., measure serum triglycerides and/or plasma free fatty acid levels). If signs of poor clearance of lipids from the circulation occur, stop the infusion and initiate a medical evaluation [see Warnings and Precautions (5.4, 5.6) and Overdosage (10)].

5.2 Hypersensitivity Reactions

Omegaven contains fish oil and egg phospholipids, which may cause hypersensitivity reactions. In postmarketing experience, anaphylaxis has been reported following Omegaven administration [see Adverse Reactions (6.2)].

Omegaven is contraindicated in patients with known hypersensitivity to fish or egg protein or to any of the active or inactive ingredients in Omegaven [see Contraindications (4)]. If a hypersensitivity reaction occurs, stop infusion of Omegaven immediately and initiate appropriate treatment and supportive measures.

5.3 Infections

Lipid emulsions, such as Omegaven, can support microbial growth and are an independent risk factor for the development of bloodstream infections. The risk of infection is increased in patients with malnutrition-associated immunosuppression, long-term use and poor maintenance of intravenous catheters, or immunosuppressive effects of other conditions or concomitant drugs.

To decrease the risk of infectious complications, ensure aseptic technique in catheter placement and maintenance, as well as in the preparation and administration of Omegaven.

Monitor for signs and symptoms of early infections including fever and chills, laboratory test results that might indicate infection (including leukocytosis and hyperglycemia), and frequently inspect the intravenous catheter insertion site for edema, redness, and discharge.

5.4 Fat Overload Syndrome

Fat overload syndrome is a rare condition that has been reported with intravenous lipid emulsions. A reduced or limited ability to metabolize lipids accompanied by prolonged plasma clearance may result in this syndrome, which is characterized by a sudden deterioration in the patient's condition including fever, anemia, leukopenia, thrombocytopenia, coagulation disorders, hyperlipidemia, hepatomegaly, deteriorating liver function, and central nervous system manifestations (e.g., coma). The cause of fat overload syndrome is unclear. Although it has been most frequently observed when the recommended lipid dose was exceeded, cases have also been described where the formulation was administered according to instructions. The syndrome is usually reversible when the infusion of the lipid emulsion is stopped.

5.5 Refeeding Syndrome

Administering PN to severely malnourished patients may result in refeeding syndrome, which is characterized by the intracellular shift of potassium, phosphorus, and magnesium as the patient becomes anabolic. Thiamine deficiency and fluid retention may also develop. To prevent these complications, closely monitor severely malnourished patients and slowly increase their nutrient intake.

5.6 Hypertriglyceridemia

Impaired lipid metabolism with hypertriglyceridemia may occur in conditions such as inherited lipid disorders, obesity, diabetes mellitus, and metabolic syndrome. Serum triglyceride levels greater than 1,000 mg/dL have been associated with an increased risk of pancreatitis [see Contraindications (4)].

To evaluate the patient's capacity to metabolize and eliminate the infused lipid emulsion, measure serum triglycerides before the start of infusion (baseline value), and regularly throughout treatment.

If hypertriglyceridemia (triglycerides greater than 250 mg/dL in neonates and infants or greater than 400 mg/dL in older children) develops, consider stopping the administration of Omegaven for 4 hours and obtain a repeat serum triglyceride level. Resume Omegaven based on new result as indicated [see Dosage and Administration (2.3)].

5.7 Aluminum Toxicity

Omegaven contains no more than 25 mcg/L of aluminum. Aluminum may reach toxic levels with prolonged parenteral administration if kidney function is impaired. Preterm infants are particularly at risk because their kidneys are immature, and they require large amounts of calcium and phosphate solutions, which contain aluminum.

Patients with impaired kidney function, including preterm infants, who receive parenteral levels of aluminum at greater than 4 to 5 mcg/kg/day accumulate aluminum at levels associated with central nervous system and bone toxicity. Tissue loading may occur at even lower rates of administration.

5.8 Monitoring/Laboratory Tests

Routine Monitoring

Monitor fluid status closely in patients with pulmonary edema or heart failure.

Throughout treatment, monitor serum triglycerides [see Warnings and Precautions (5.7)], fluid and electrolyte status, serum osmolarity, blood glucose, liver and kidney function, blood count (including platelets), and coagulation parameters.

The lipids contained in Omegaven may interfere with the results of some laboratory tests (e.g., hemoglobin, lactate dehydrogenase, bilirubin, oxygen saturation) if the blood is sampled before the lipids have cleared from the bloodstream. Conduct these tests at least 6 hours after stopping the infusion.

Omegaven contains Vitamin K that may counteract anticoagulant activity [see Drug Interactions (7)].

Essential Fatty Acids

Monitoring patients for signs and symptoms of essential fatty acid deficiency (EFAD) is recommended. Laboratory tests are available to determine serum fatty acids levels. Reference values should be consulted to help determine adequacy of essential fatty acid status. Increasing essential fatty acid intake (enterally or parenterally) is effective in treating and preventing EFAD.

6 ADVERSE REACTIONS

The following clinically significant adverse reactions are described elsewhere in the labeling:

- Clinical Decompensation with Rapid Infusion of Intravenous Lipid Emulsion in Neonates and Infants [see Warnings and Precautions (5.1)]
- Hypersensitivity reactions [see Warnings and Precautions (5.2)]
- Infections [see Warnings and Precautions (5.3)]
- Fat overload syndrome [see Warnings and Precautions (5.4)]
- Refeeding syndrome [see Warnings and Precautions (5.5)]
- Hypertriglyceridemia [see Warnings and Precautions (5.6)]
- Aluminum toxicity [see Warnings and Precautions (5.7)]

6.1 Clinical Trials Experience

Because clinical trials are conducted under widely varying conditions, adverse reaction rates observed in the clinical trials of a drug cannot be directly compared to rates in the clinical trials of another drug and may not reflect the rates observed in practice.

The safety database for Omegaven reflects exposure in 189 pediatric patients (19 days to 15 years of age) treated for a median of 14 weeks (3 days to 8 years) in two clinical trials. Omegaven was administered at a maximum dose of 1 g/kg/day as the lipid component of a PN regimen which also included dextrose, amino acids, vitamins, and trace elements; 158 (84%) of these patients received concurrent lipids from enteral nutrition [see Clinical Studies (14)].

Adverse reactions that occurred in more than 5% of patients who received Omegaven and with a higher incidence than the comparator group are shown in Table 2. Patients had a complicated medical and surgical history prior to receiving Omegaven treatment and the mortality was 13%. Underlying clinical conditions prior to the initiation of Omegaven therapy included prematurity, low birth weight, necrotizing enterocolitis, short bowel syndrome, ventilator dependence, coagulopathy, intraventricular hemorrhage, and sepsis.

Table 2: Adverse Reactions in Greater Than 5% of Omegaven-Treated Pediatric Patients with PNAC
Adverse Reaction | Omegaven (N=189) n (%)
Vomiting | 87 (46)
Agitation | 67 (35)
Bradycardia | 66 (35)
Apnea | 38 (20)
Viral Infection | 30 (16)
Erythema | 23 (12)
Rash | 15 (8)
Abscess | 14 (7)
Neutropenia | 13 (7)
Hypertonia | 11 (6)
Incision site erythema | 11 (6)

Twelve (6%) Omegaven-treated patients were listed for liver transplantation (1 patient was listed 18 days before treatment, and 11 patients after a median of 42 days [range: 2 days to 8 months] of treatment); 9 (5%) received a transplant after a median of 121 days (range: 25 days to 6 months) of treatment, and 3 (2%) were taken off the waiting list because cholestasis resolved.

One hundred thirteen (60%) Omegaven-treated patients reached DBil levels less than 2 mg/dL and AST or ALT levels less than 3 times the upper limit of normal, with median AST and ALT levels for Omegaven-treated patients at 89 and 65 U/L, respectively, by the end of the study.

Median hemoglobin levels and platelet counts for Omegaven-treated patients at baseline were 10.2 g/dL and 173 × 10^9/L, and by the end of the study these levels were 10.5 g/dL and 217 × 10^9/L, respectively. Adverse reactions associated with bleeding were experienced by 74 (39%) of Omegaven-treated patients.

Median glucose levels at baseline and the end of the study were 86 and 87 mg/dL for Omegaven-treated patients, respectively. Hyperglycemia was experienced by 13 (7%) Omegaven-treated patients.

Median triglyceride levels at baseline and the end of the study were 121 mg/dL and 72 mg/dL for Omegaven-treated patients respectively. Hypertriglyceridemia was experienced by 5 (3%) Omegaven-treated patients.

The triene:tetraene (Mead acid:arachidonic acid) ratio was used to monitor essential fatty acid status in Omegaven-treated patients only in Study 1 (n = 123) [see Warnings and Precautions (5.8)]. The median triene:tetraene ratio was 0.02 (interquartile range: 0.01 to 0.03) at both baseline and the end of the study. Blood samples for analysis may have been drawn while the lipid emulsion was being infused and patients received enteral or oral nutrition.

6.2 Postmarketing Experience

The following adverse reactions have been identified during post-approval use of Omegaven. Because these reactions were reported voluntarily from a population of uncertain size, it is not always possible to reliably estimate their frequency or establish a causal relationship to drug exposure.

Hematologic system disorders: hemorrhage

Immune system disorders: hypersensitivity reactions, including anaphylaxis [see Contraindications (4), Warnings and Precautions (5.2)]

7 DRUG INTERACTIONS

7.1 Antiplatelet Agents and Anticoagulants

Some published studies have demonstrated prolongation of bleeding time in patients taking antiplatelet agents or anticoagulants and oral omega-3 fatty acids. The prolongation of bleeding times reported in those studies did not exceed normal limits and there were no clinically significant bleeding episodes. Nonetheless, it is recommended to periodically monitor bleeding time in patients receiving Omegaven and concomitant antiplatelet agents or anticoagulants.

8 USE IN SPECIFIC POPULATIONS

8.1 Pregnancy

Risk Summary

There are no available data on Omegaven use in pregnant women to establish a drug- associated risk of major birth defects, miscarriage, or adverse maternal or fetal outcomes. Animal reproduction studies have not been conducted with fish oil triglycerides.

The estimated background risk of major birth defects and miscarriage in the indicated population is unknown. All pregnancies have a background risk of birth defect, loss, or other adverse outcomes. In the US general population, the estimated background risk of major birth defects and miscarriage in clinically recognized pregnancies is 2% to 4% and 15% to 20%, respectively.

8.2 Lactation

Risk Summary

No data are available regarding the presence of fish oil triglycerides from Omegaven in human milk, the effects on the breastfed infant, or the effects on milk production. Lactating women receiving oral omega-3 fatty acids have been shown to have higher levels of omega-3 fatty acids in their milk. The developmental and health benefits of breastfeeding should be considered along with the mother's clinical need for Omegaven, and any potential adverse effects of Omegaven on the breastfed infant.

8.4 Pediatric Use

The effectiveness of Omegaven was established in two open-label clinical trials of 82 pediatric patients, 3 to 42 weeks of age, including preterm neonates with estimated gestational age of greater than 24 weeks at birth. Patients administered Omegaven attained and maintained growth through at least 108 weeks of treatment [see Clinical Studies (14)].

The safety of Omegaven was established in 189 pediatric patients (19 days to 15 years of age). The most common adverse reactions in Omegaven-treated patients were vomiting, agitation, and bradycardia [see Adverse Reactions (6.1)].

In the postmarketing setting, clinical decompensation with rapid infusion of intravenous lipid emulsion in neonates and infants, sometimes fatal has been reported [see Warnings and Precautions (5.1)].

Preterm neonates and infants who receive treatment with Omegaven may be at risk of aluminum toxicity and other metabolic abnormalities [see Warnings and Precautions (5.7, 5.8)].

8.5 Geriatric Use

Clinical trials of Omegaven did not include patients 65 years of age and older.

10 OVERDOSAGE

In the event of an overdose, serious adverse reactions may occur [see Warnings and Precautions (5.1, 5.4)]. Stop the infusion of Omegaven until triglyceride levels have normalized and any symptoms have abated. The effects are usually reversible by stopping the lipid infusion. If medically appropriate, further intervention may be indicated. Lipids are not dialyzable from serum.

11 DESCRIPTION

Omegaven (fish oil triglycerides) is a sterile, nonpyrogenic, white, homogenous emulsion for intravenous infusion as a supply of calories in patients with PNAC. Each mL of Omegaven contains 0.1 g of fish oil, 0.012 g egg phospholipids, 0.025 g glycerin, 0.15 to 0.3 mg dl-alpha-tocopherol, 0.3 mg sodium oleate, water for injection, and sodium hydroxide for pH adjustment (pH 6 to 9). The phosphate content is 0.015 mmol/mL.

The fish oil included in Omegaven is a triglyceride mixture consisting of esters of long-chain saturated fatty acids and unsaturated fatty acids with the following structure:

where , , and are long chain acyl groups. Because triglycerides often contain different long chain fatty acids at each position, possible structures can have molecular weights ranging from 700 to 1000 g/mol. The main fatty acid components of the fish oil in Omegaven are EPA (13% to 26%) and DHA (14% to 27%). The fish oil also contains palmitic acid (4% to 12%), oleic acid (4% to 11%), palmitoleic acid (4% to 10%), myristic acid (2% to 7%), and arachidonic acid (0.2% to 2.0%). Additionally, the mean contents of linoleic acid and alpha-linolenic acid are 1.5% and 1.1%, respectively. The fish oil component has a total omega-3 fatty acid content of 40% to 54%. The empirical formula, molecular weight, and chemical structure of the main fatty acid components are:

EPA C20H30O2 302.45

DHA C22H32O2 328.49

Palmitic acid C16H32O2 256.43

Oleic acid C18H34O2 282.47

Palmitoleic acid C16H30O2 254.41

Linoleic acid C18H32O2 280.45

Myristic acid C14H28O2 228.38

Arachidonic acid C20H32O2 304.47

Alpha-linolenic acid C18H30O2 278.44

Omegaven 5 g/50 mL contains 5 grams of fish oil and 0.6 g egg phospholipids, 1.25 g glycerin, 7.5 to 15 mg dl-alpha-tocopherol, 0.015 g sodium oleate, water for injection, and sodium hydroxide for pH adjustment (pH 6 to 9) packaged in a single-dose 50-mL glass bottle enclosed with a rubber stopper. The phosphate content of the drug product is 0.75 mmol.

The mean content of the two major fatty acid components in 50 mL are 1.0 g EPA (range: 0.6 to 1.5 g) and 0.96 g DHA (range: 0.7 to 1.7 g). Additionally, the mean content of linoleic acid, alphalinolenic acid, and arachidonic acid per 50 mL are 0.16 g, 0.07 g, and 0.13 g, respectively.

Omegaven 10 g/100 mL contains 10 grams of fish oil and 1.2 g egg phospholipids, 2.5 g glycerin, 15 to 30 mg dl-alpha-tocopherol, 0.03 g sodium oleate, water for injection, and sodium hydroxide for pH adjustment (pH 6 to 9) packaged in a single-dose 100-mL glass bottle enclosed with rubber stopper. The phosphate content of the drug product is 1.5 mmol. The mean content of the two major fatty acid components in 100 mL are 2.0 g EPA (range: 1.2 to 3.0 g) and 1.9 g DHA (range: 1.3 to 3.3 g). Additionally, the mean content of linoleic acid, alpha-linolenic acid, and arachidonic acid per 100 mL are 0.31g, 0.13 g, and 0.25 g; respectively.

The total energy content of Omegaven is 112 kcal/100 mL (1.12 kcal/mL), including lipids, phospholipids, and glycerol.

Omegaven has an osmolality of approximately 342 mOsm/kg water (which represents an osmolarity of 273 mOsm/L).

Omegaven contains no more than 25 mcg/L of aluminum.

12 CLINICAL PHARMACOLOGY

12.1 Mechanism of Action

Omegaven provides a biologically utilizable source of calories and essential fatty acids.

Fatty acids serve as an important substrate for energy production. The most common mechanism of action for energy production derived from fatty acid metabolism is beta oxidation. Fatty acids are also important for membrane structure and function, as precursors for bioactive molecules (such as prostaglandins), and as regulators of gene expression.

12.3 Pharmacokinetics

The plasma concentrations of EPA and DHA, the major fatty acids in Omegaven, as well as linoleic acid and alpha-linolenic acid (essential fatty acids) were measured along with the markers of essential fatty acid status in 58 pediatric patients with PNAC after an intravenous infusion of 1 mg/kg/day of Omegaven over 10 weeks. Five patients received Omegaven as the exclusive lipid source, and all others received concurrent enteral or oral nutrition.

Figure 1: Mean Plasma Concentrations of Fatty Acids Over 10 Weeks of Omegaven Infusion in Pediatric Patients with PNAC

Error bars represent ± 1 standard deviation (SD).

Numbers at the top of plots represent the number of patients at each time point

If more than one value was available for a patient at any given time point, the average was used.

13 NONCLINICAL TOXICOLOGY

13.1 Carcinogenesis, Mutagenesis, Impairment of Fertility

No studies have been performed with fish oil triglycerides to evaluate the carcinogenic potential or its effect on fertility.

Fish oil triglycerides was negative in the bacterial mutagenicity test with Salmonella typhimurium and the hypoxanthine phosphoribosyl transferase (HPRT) gene mutation assay in Chinese hamster V79 cells. Fish oil triglycerides was not clastogenic in cultured human peripheral lymphocytes or in a rat bone marrow cytogenetic study.

14 CLINICAL STUDIES

The efficacy of Omegaven was evaluated in two open-label single-center clinical trials (Study 1, NCT00910104, and Study 2, NCT00738101) in pediatric patients with PNAC (defined as direct or conjugated bilirubin [DBil] equal to or greater than 2 mg/dL) who required PN for at least 14 days. Although Study 1 and Study 2 were not adequately designed to demonstrate noninferiority or superiority of Omegaven to the soybean oil-based lipid emulsion comparator, the data from these studies support Omegaven as a source of calories in pediatric patients with PNAC. Nutritional efficacy was assessed by biomarkers of lipid metabolism, growth indices (body weight, length/height and head circumference), and/or mean changes in fatty acid parameters.

Both trials prospectively enrolled Omegaven-treated patients (maximum dose of 1 g/kg/day) and used historical control patients who received a soybean oil-based lipid emulsion (maximum dose of 3 g/kg/day) as a comparator. Patients were expected to require PN, which also included dextrose, amino acids, vitamins and trace elements, for at least 30 days (Study 1) or 14 days (Study 2), had PNAC, and had received standard therapies to prevent progression of liver disease. Study 1 enrolled patients less than 2 years of age and Study 2 enrolled patients less than 5 years of age. Patients with another cause of chronic liver disease (in the absence of intestinal failure) were excluded. Patients with an international normalized ratio (INR) greater than 2 and patients with portal vein thrombosis or reversal of portal flow by abdominal ultrasound were also excluded.

For the efficacy analyses of Studies 1 and 2, Omegaven-treated patients were pair-matched in a 2:1 manner to historical control patients primarily based on DBil levels and postmenstrual age at baseline. There were 123 patients (82 Omegaven; 41 historical control) in this population, 78 (52; 26) were from Study 1, and 45 (30; 15) were from Study 2. A summary of concurrent enteral/oral nutrition intake for each study is provided in Table 3.

Table 3: Summary of Median Enteral or Oral Intakes in Pediatric Patients with PNAC in Study 1 and Study 2
Parameter | Study 1 |  | Study 2
Parameter | Omegaven (n=50) a | Historical Control (n=26) | Omegaven (n=30) | Historical Control (n=15)
Number of patients who received concurrent enteral or oral nutrition | 44 (88%) | 26 (100%) | 24 (80%) | 14 (93%)
Percentage of total calories provided enterally or orally, median (Min - Max) | 24% (1% – 53%) | 25% (0.4% – 68%) | 21% (1% – 75%) | 12% (3% – 40%)
a. Two Omegaven-treated patients in Study 1 did not have data regarding enteral or oral intakes.

In the combined efficacy analysis population from Study 1 and Study 2, median chronological age was 9 weeks (range: 3 to 42 weeks) in the Omegaven group and 7 weeks (range: 0 to 41 weeks) in the historical control group. The majority of these patients were preterm infants at birth (90% Omegaven; 83% historical control), with gestational age categories as follows: extremely preterm (31%; 20%); very preterm (20%; 24%); moderate or late preterm (40%; 39%). A majority of patients were also considered to have low, very-low, or extremely-low birth weights (76%; 82%), with birth weight categories as follows: extremely-low birth weight (34%; 24%); very-low birth weight (17%; 21%); low birth weight (25%; 37%).

The efficacy analysis population had more males (51%; 59%) than females, and the majority of patients were White (60%; 66%).

At baseline, the median age-adjusted body weight (Z-score) was -1.3 for the Omegaven group and -1.1 for the historical control group; 27% and 28% were low-for-age in body weight, 43% and 40% were low-for-age in body height/length, and 25% and 15% were low-for-age in head circumference for the Omegaven and historical control groups, respectively (low-for-age corresponded to Z-scores less than or equal to -1.9 for each growth parameter). In the efficacy analysis population, baseline median DBil, AST, and ALT levels were 3.8 mg/dL, 101 U/L, and 67 U/L, respectively, for the Omegaven group; and 3.8 mg/dL, 115 U/L, and 52 U/L, respectively, for the historical control group.

The median (range) of the duration of treatment was 2.7 months (5 days to 8 years) for the Omegaven group and 3.6 months (16 days to 2 years) for the historical control group.

The changes in median age-adjusted body weight (Z-scores) over time for Omegaven- treated patients (Figure 2) appeared similar to those for historical control patients. In both the Omegaven and historical control groups, there was an initial decline in all growth parameters (weight, height/length, head circumference) over the initial weeks of treatment, followed by catch-up growth and more age-appropriate values through the remainder of the study. By comparing the Omegaven study data to age-standardized Fenton and World Health Organization (WHO) growth charts to assess age appropriate growth in patients with PNAC, patients treated with Omegaven as their exclusive lipid source also achieved age- appropriate growth.

Figure 2: Median Age-Adjusted Body Weight (Z-scores) Over Time in Omegaven- Treated Pediatric Patients with PNAC in Study 1 and Study 2*

BL = baseline

Error bars represent interquartile ranges.

*Data from pair-matched Omegaven patients were truncated at week 132. Median values are only shown for visits with data from at least 2 patients at a particular visit.

In the combined analysis from Study 1 and Study 2, the number of Omegaven and historical control patients who achieved full enteral feeding by the end of the study was 52 (63%) patients and 24 (59%) patients, respectively. The median time to full enteral feeding was approximately 15 weeks for both groups.

At the end of the studies, the median DBil level for Omegaven-treated patients was 0.60 mg/dL (interquartile range: 0.1 to 2.8 mg/dL). The Kaplan-Meier estimate of the median time for DBil values to return to less than 2.0 mg/dL was approximately 5.7 weeks [see Dosage and Administration (2.3), Adverse Reactions (6.1)].

16 HOW SUPPLIED/STORAGE AND HANDLING

Omegaven (fish oil triglycerides) injectable emulsion, 5 g/50 mL and 10 g/100 mL (0.1 g/mL) is a white, homogenous, sterile emulsion supplied as follows:

50 mL single-dose glass bottle | NDC 63323-205-21
Carton of 10 x 50 mL | NDC 63323-205-50
100 mL single-dose glass bottle | NDC 63323-205-31
Carton of 10 x 100 mL | NDC 63323-205-00

The stopper used as the bottle closure is not made with natural rubber latex, PVC, or DEHP.

Storage and Handling

Store below 25°C (77°F). Avoid excessive heat. Do not freeze. If accidentally frozen, discard product.

Once the bottle is connected to the infusion set, use Omegaven immediately. Complete infusion within 12 hours when using a Y-connector [see Dosage and Administration (2.1)].

Infuse admixtures containing Omegaven immediately. If not used immediately, admixtures can be stored for up to 6 hours at room temperature or up to 24 hours under refrigeration. Complete the infusion within 24 hours after removal from storage [see Dosage and Administration (2.2)].

17 PATIENT COUNSELING INFORMATION

When initiating Omegaven administration, discuss the following information:

Clinical Decompensation with Rapid Infusion of Intravenous Lipid Emulsion in Neonates and Infants

Inform caregivers that acute respiratory distress and death may occur in neonates and infants after rapid infusion of intravenous lipid emulsions. If Omegaven is infused at home, instruct caregivers not to exceed the maximum infusion rate [see Warnings and Precautions (5.1)].

Hypersensitivity reactions

Inform caregivers that Omegaven may cause hypersensitivity reactions, including anaphylaxis. If Omegaven is infused at home, instruct caregivers to stop the infusion of Omegaven immediately and seek medical attention if they experience signs or symptoms of a hypersensitivity reaction, such as rapid or weak heartbeat, feeling faint, difficulty in breathing or swallowing, vomiting, nausea, headache, sweating, dizziness, hives, rash, itching, flushing, dizziness, fever, or chills [see Warnings and Precautions (5.2)].

Infections

Inform caregivers that patients who receive Omegaven are at risk of infection. If Omegaven is infused at home, instruct caregivers to ensure aseptic techniques are used for the preparation and administration of Omegaven and to monitor for signs and symptoms of infection [see Warnings and Precautions (5.3)].

Fat overload syndrome

Inform caregivers that fat overload syndrome has been reported with the use of intravenous lipid emulsions. If Omegaven is infused at home, instruct caregivers to stop Omegaven if signs or symptoms of fat overload syndrome occur [see Warnings and Precautions (5.4)].

Refeeding syndrome

If the patient is severely malnourished, inform caregivers that administering parenteral nutrition including Omegaven may result in refeeding syndrome [see Warnings and Precautions (5.5)].

Hypertriglyceridemia

Inform caregivers about the risk of hypertriglyceridemia with Omegaven use [see Warnings and Precautions (5.6)].

Aluminum toxicity

Inform caregivers that prolonged PN administration in patients with renal impairment, including preterm neonates, may result in aluminum reaching toxic levels associated with central nervous system and bone toxicity [see Warnings and Precautions (5.7)].

Fresenius Kabi and Omegaven are registered trademarks of Fresenius Kabi.

Manufactured by:

Graz, Austria

www.fresenius-kabi.com/us

451555C

PACKAGE LABEL

PACKAGE LABEL- PRINCIPAL DISPLAY – Omegaven 50 mL Vial Label

NDC 63323-205-21 255050

Omegaven ®

(fish oil triglycerides) Injectable emulsion

5 grams per 50 mL

(0.1 grams per mL)

Energy: 56 kcal per 50 mL

For intravenous use only. Rx only

50 mL Single-Dose bottle - Discard Unused Portion

PACKAGE LABEL

PACKAGE LABEL- PRINCIPAL DISPLAY – Omegaven 50 mL Vial Carton Label

NDC 63323-205-50 255050

Omegaven ®

(fish oil triglycerides) Injectable emulsion

5 grams per 50 mL

(0.1 grams per mL)

For intravenous use only. Rx only

Sterile.

Store below 25°C. (77°F). Do not freeze.

Use only if the emulsion is homogeneous.

See prescribing information.

Not made with natural rubber latex

10 x 50 mL

Single-Dose bottle-

Discard Unused Portion

PACKAGE LABEL

PACKAGE LABEL- PRINCIPAL DISPLAY – Omegaven 100 mL Vial Label

NDC 63323-205-31 255100

Omegaven ®

(fish oil triglycerides) Injectable emulsion

10 grams per 100 mL

(0.1 grams per mL)

Energy: 112 kcal per 100 mL

For intravenous use only. Rx only

100 mL Single-Dose bottle - Discard Unused Portion

PACKAGE LABEL

PACKAGE LABEL- PRINCIPAL DISPLAY – Omegaven 100 mL Vial Carton Label

NDC 63323-205-00 255100

Omegaven ®

(fish oil triglycerides) Injectable emulsion

10 grams per 100 mL

(0.1 grams per mL)

For intravenous use only. Rx only

Sterile.

Store below 25°C. (77°F). Do not freeze.

Use only if the emulsion is homogeneous.

See prescribing information.

Not made with natural rubber latex

10 x 100 mL Single-Dose bottle-

Discard Unused Portion